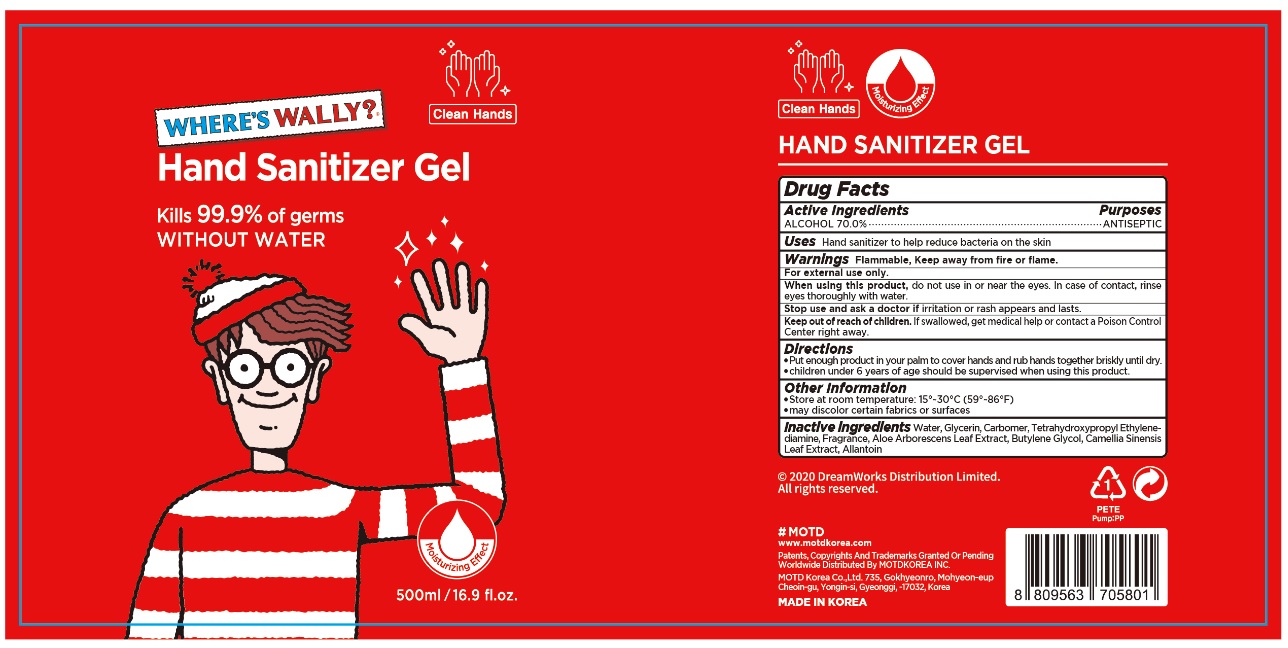 DRUG LABEL: WALLY Hand Sanitizer Gel
NDC: 74004-703 | Form: GEL
Manufacturer: Ester Co., Ltd.
Category: otc | Type: HUMAN OTC DRUG LABEL
Date: 20200521

ACTIVE INGREDIENTS: ALCOHOL 350 mL/500 mL
INACTIVE INGREDIENTS: ALLANTOIN; GREEN TEA LEAF; BUTYLENE GLYCOL; EDETOL; CARBOMER HOMOPOLYMER, UNSPECIFIED TYPE; WATER; ALOE ARBORESCENS LEAF; GLYCERIN

[Ester Co., Ltd.-WALLY Hand Sanitizer Gel] 500 ml : BOTTLE+PUMP : 74004-703-01